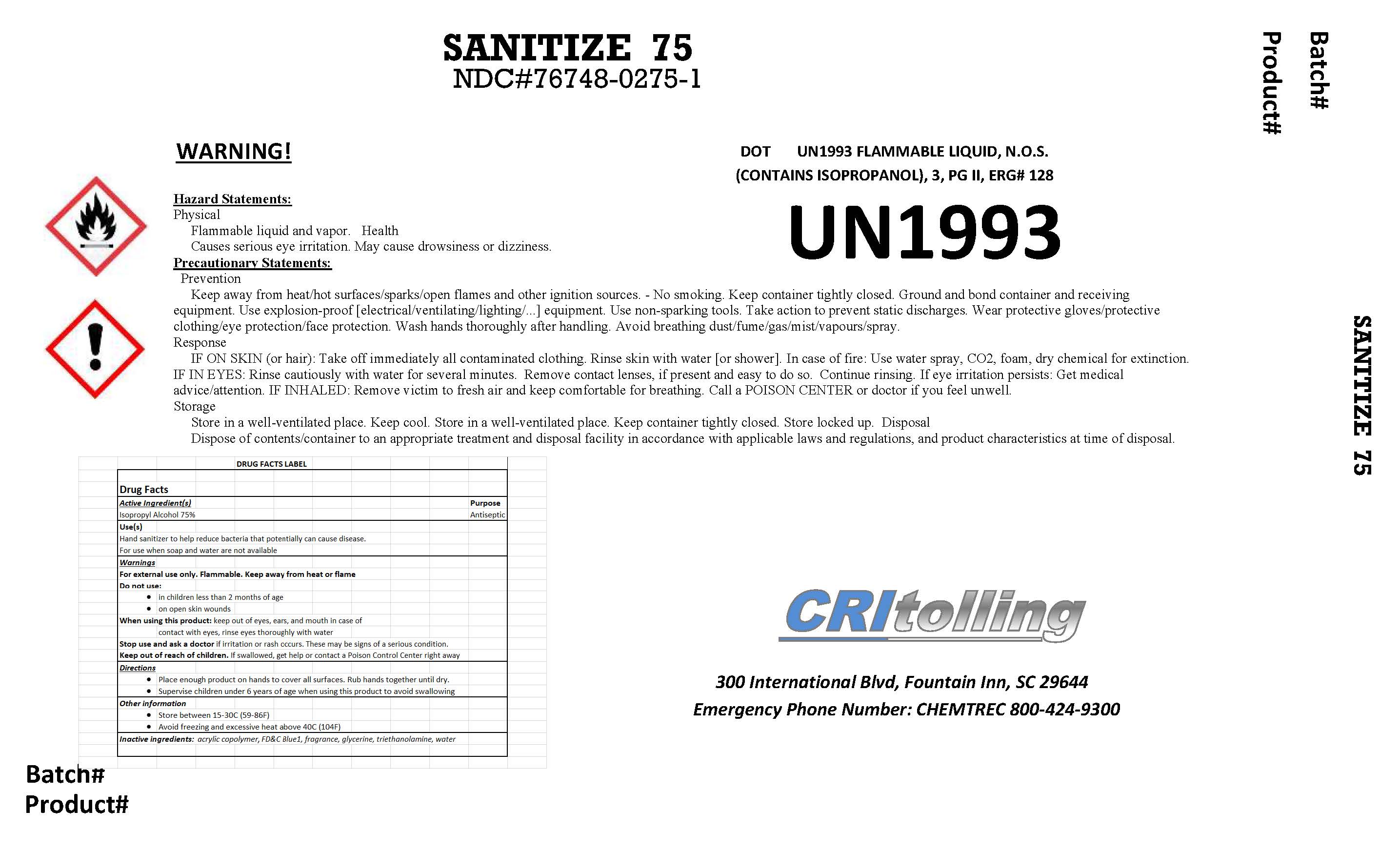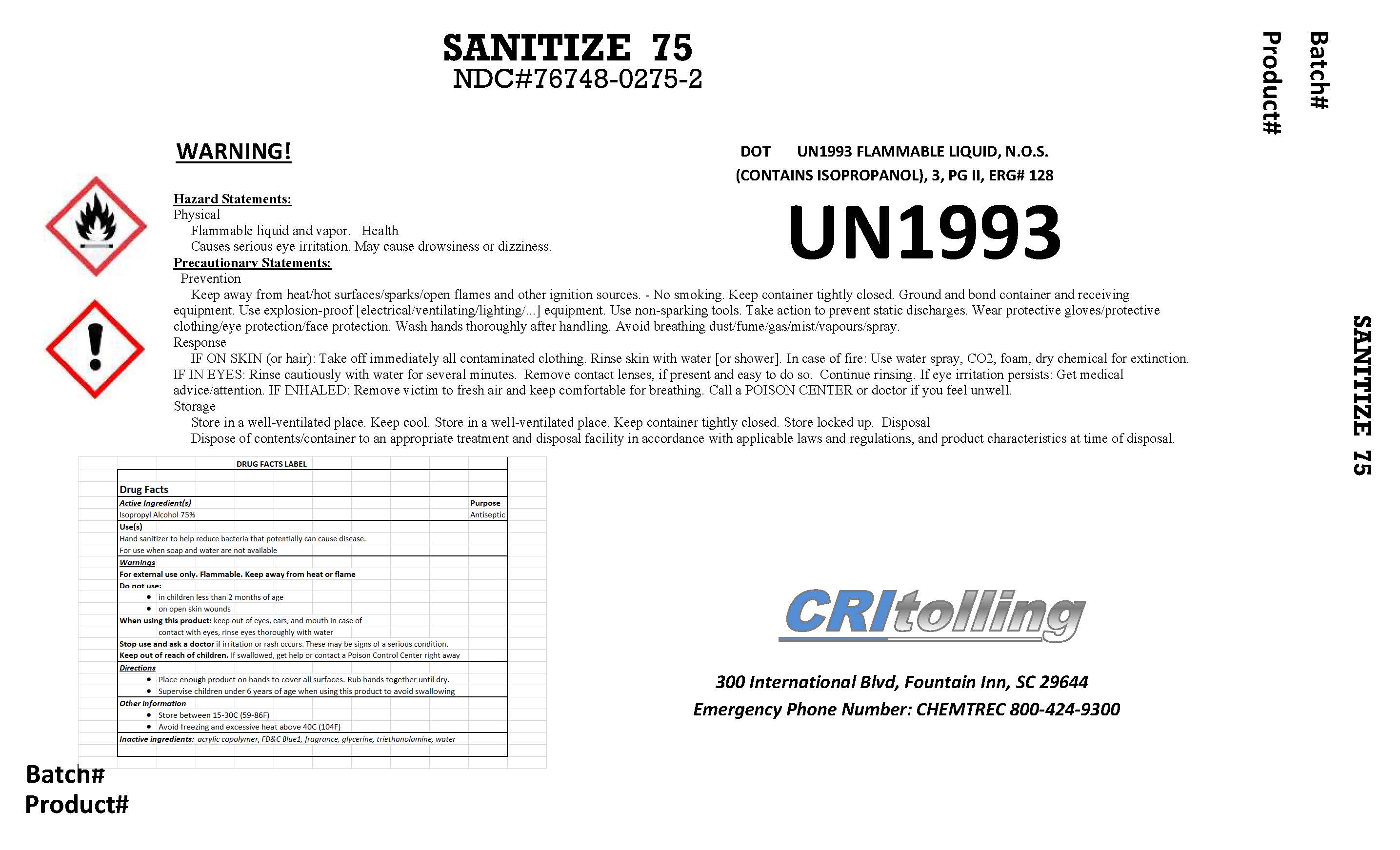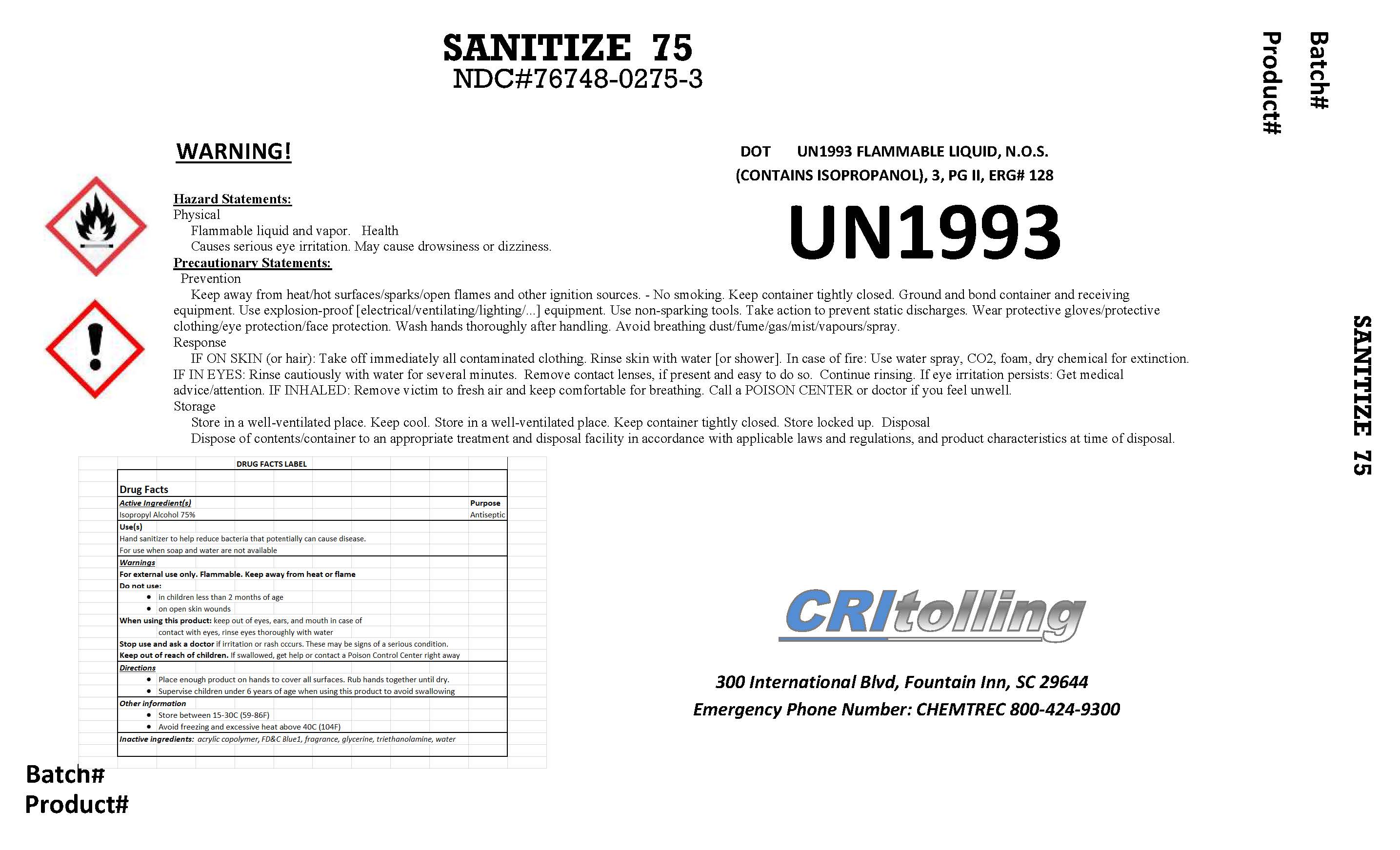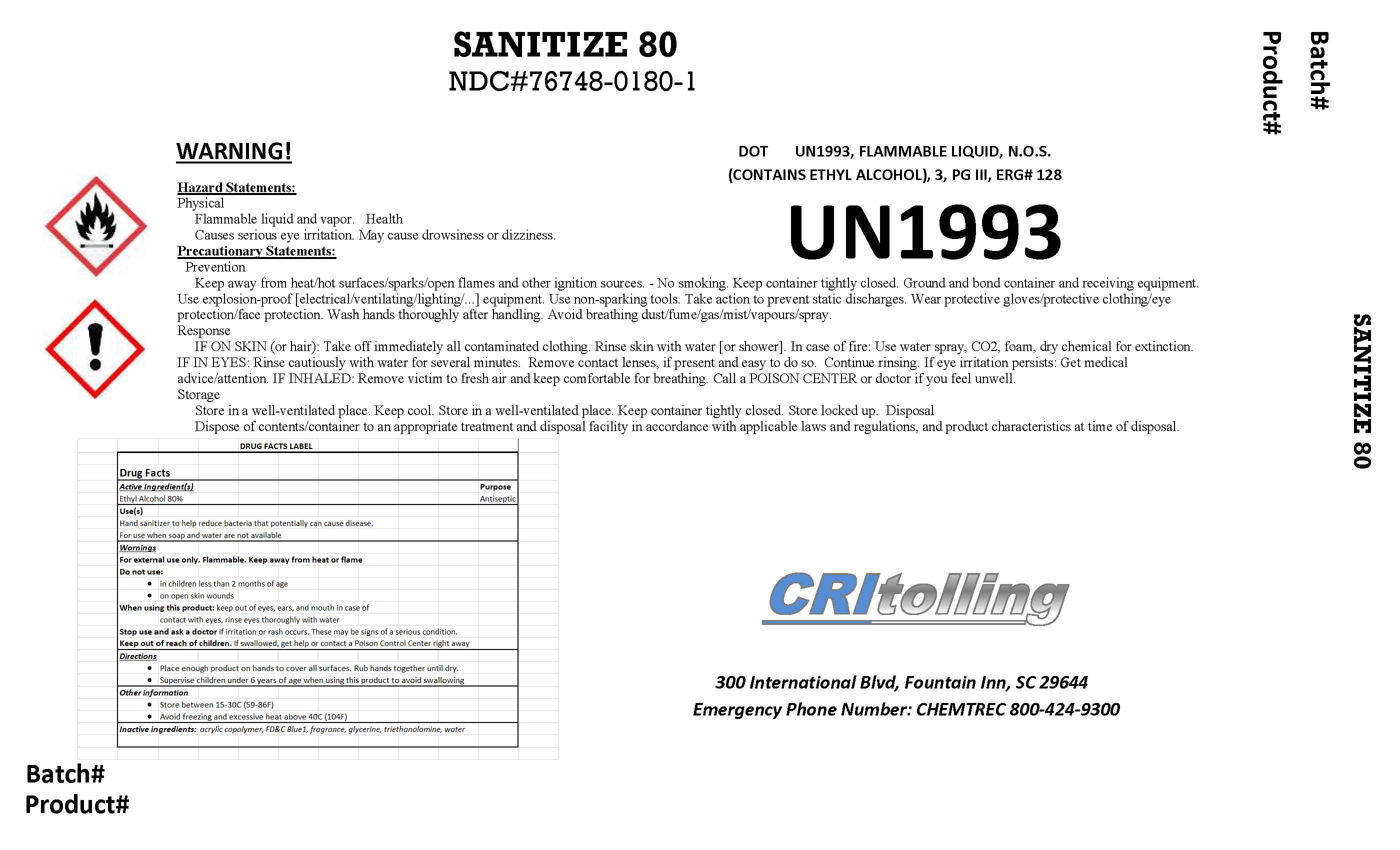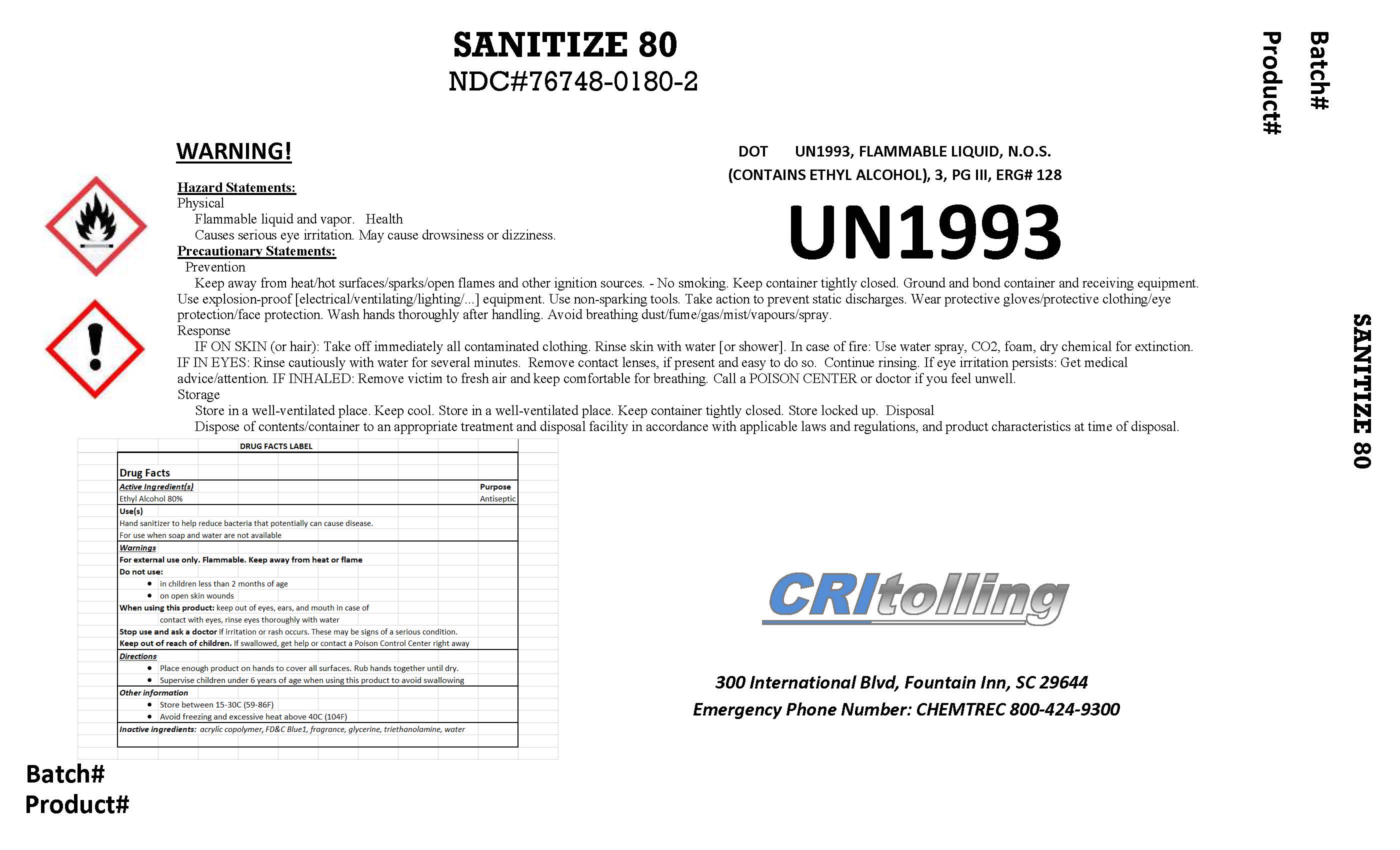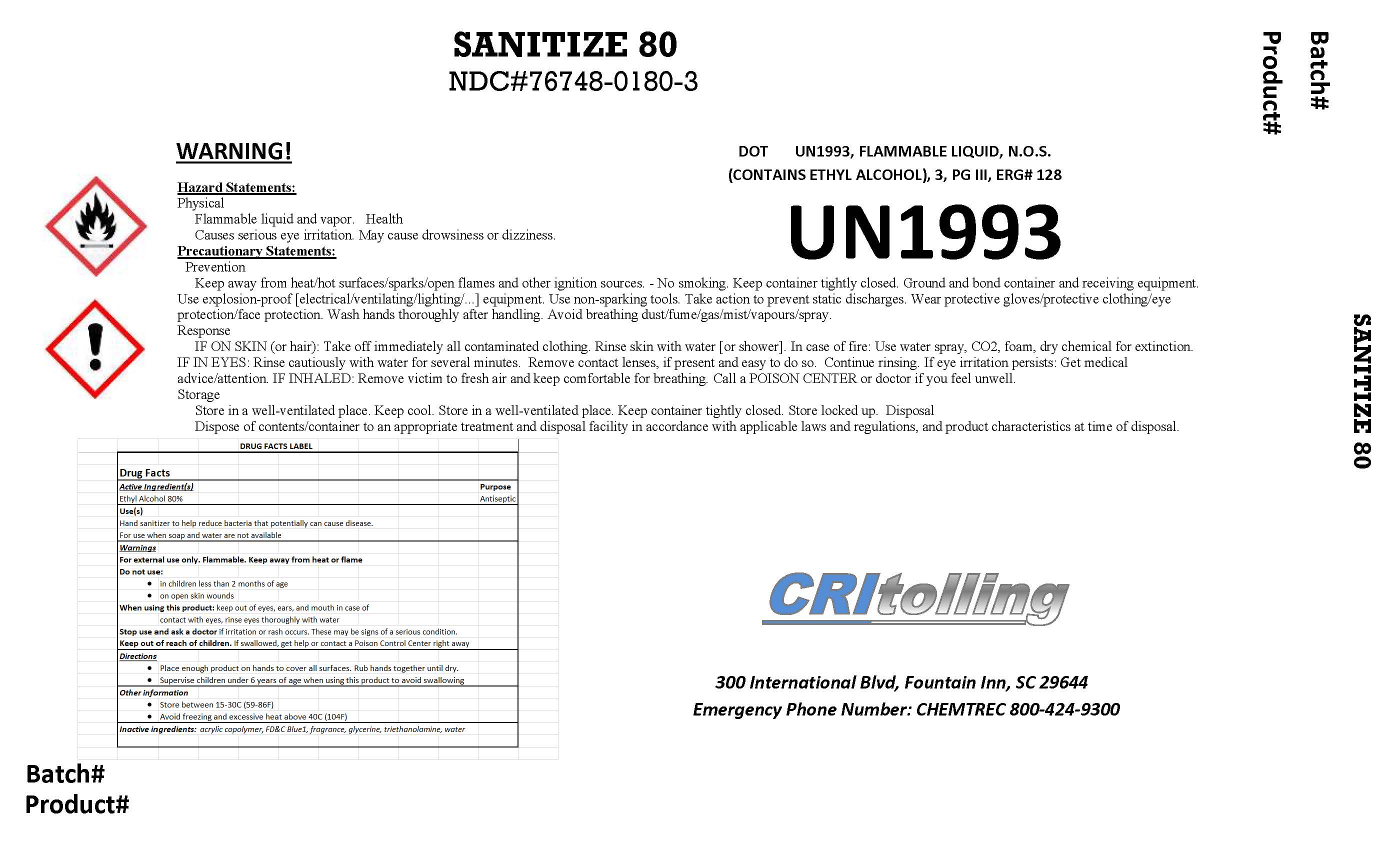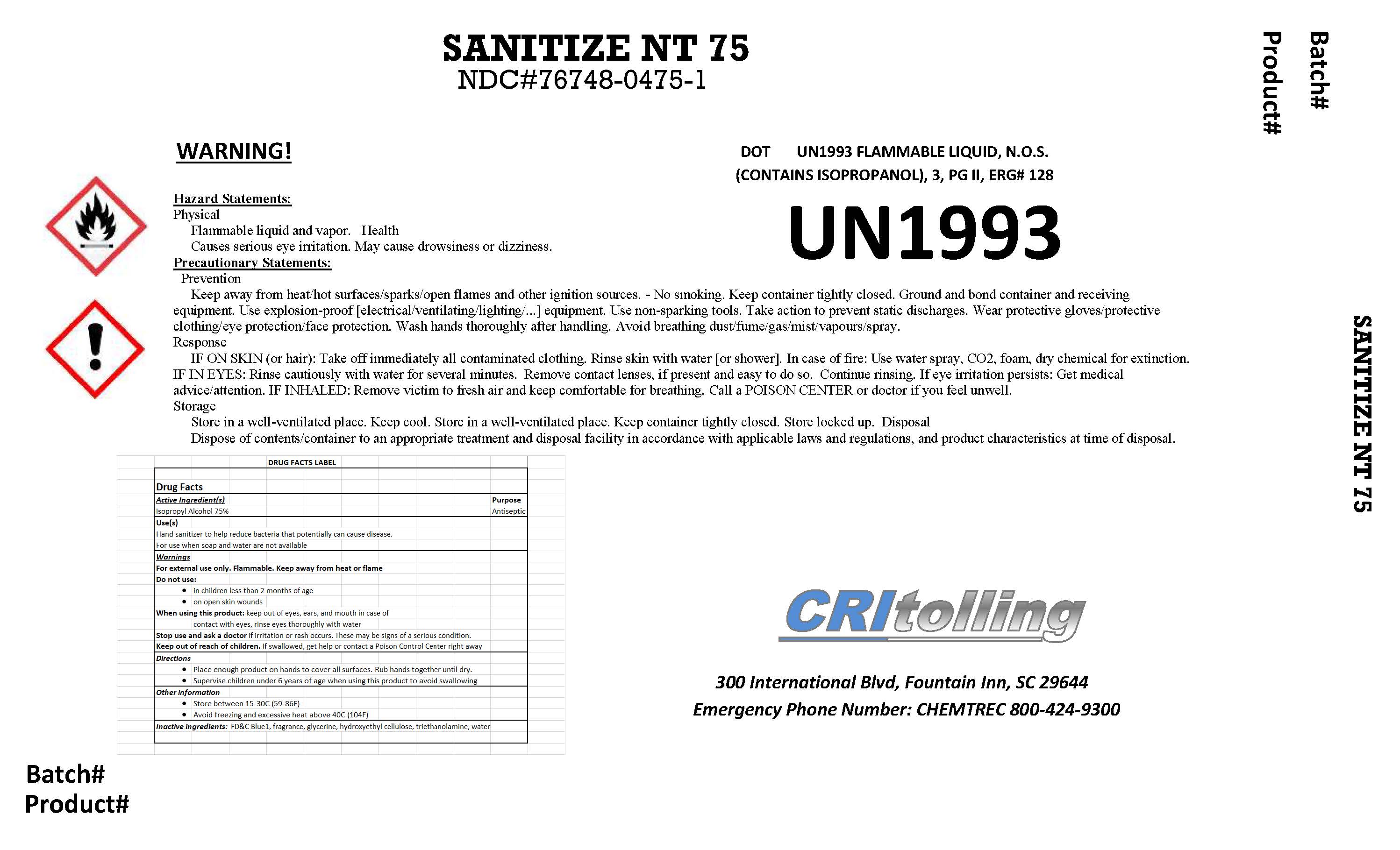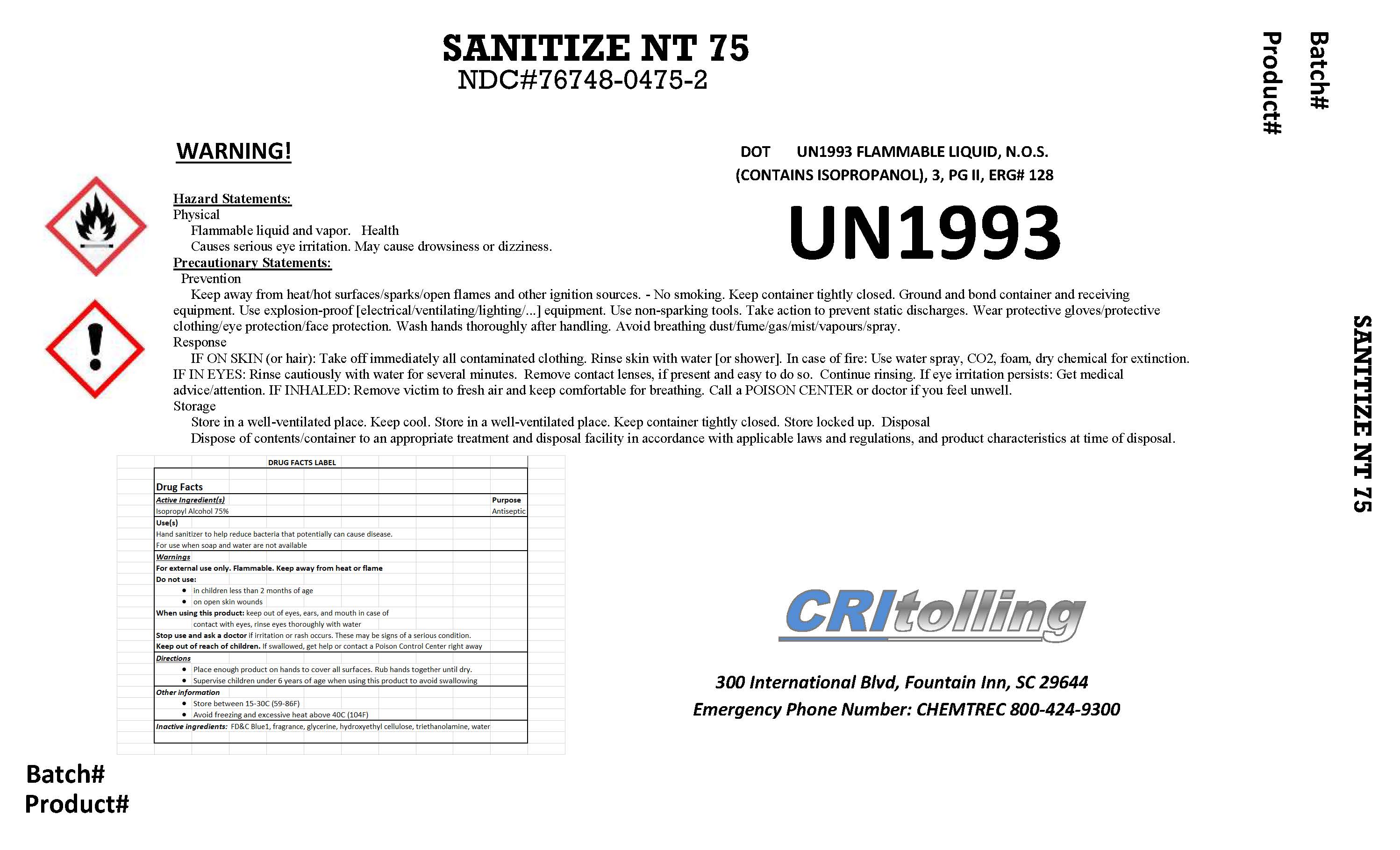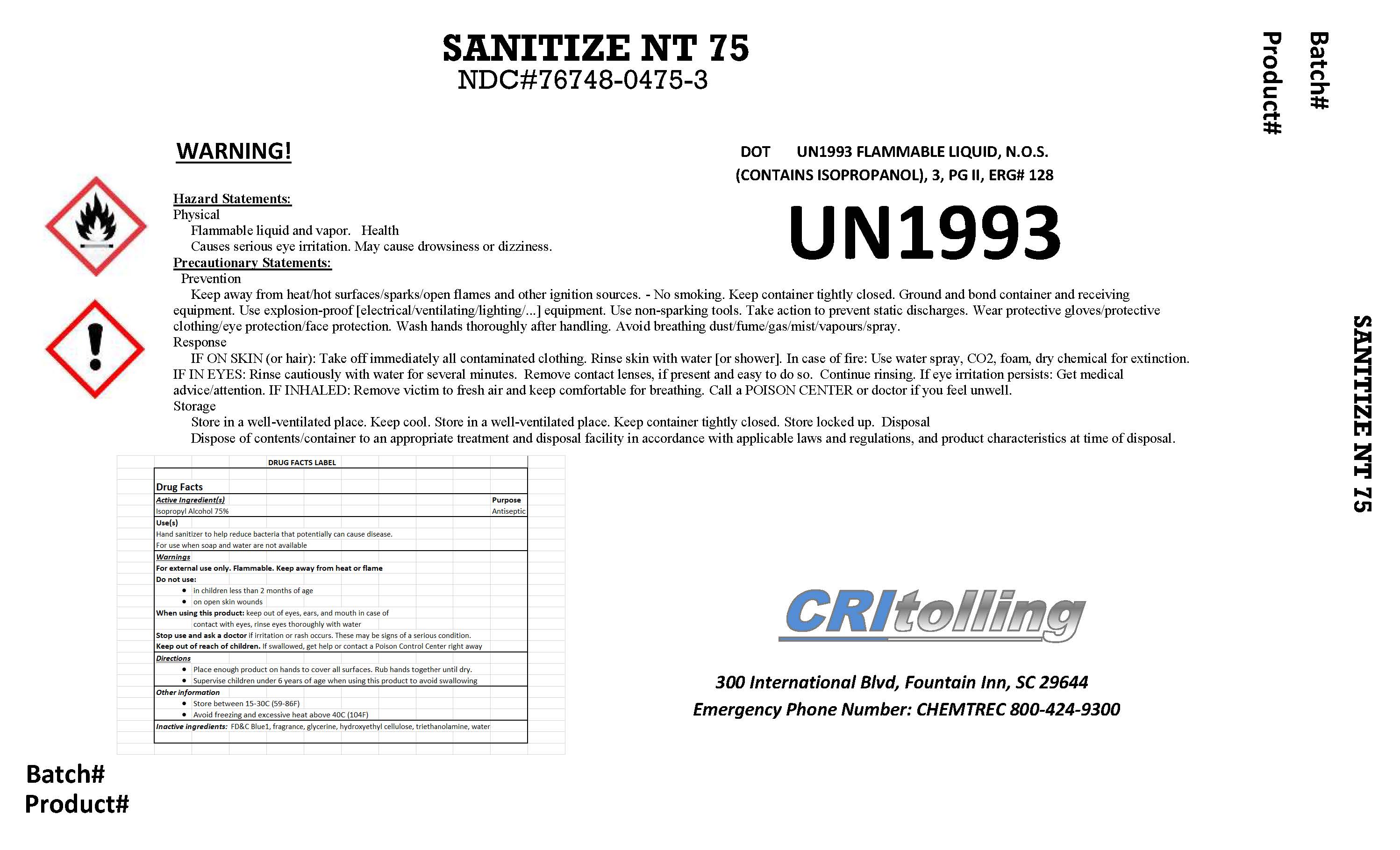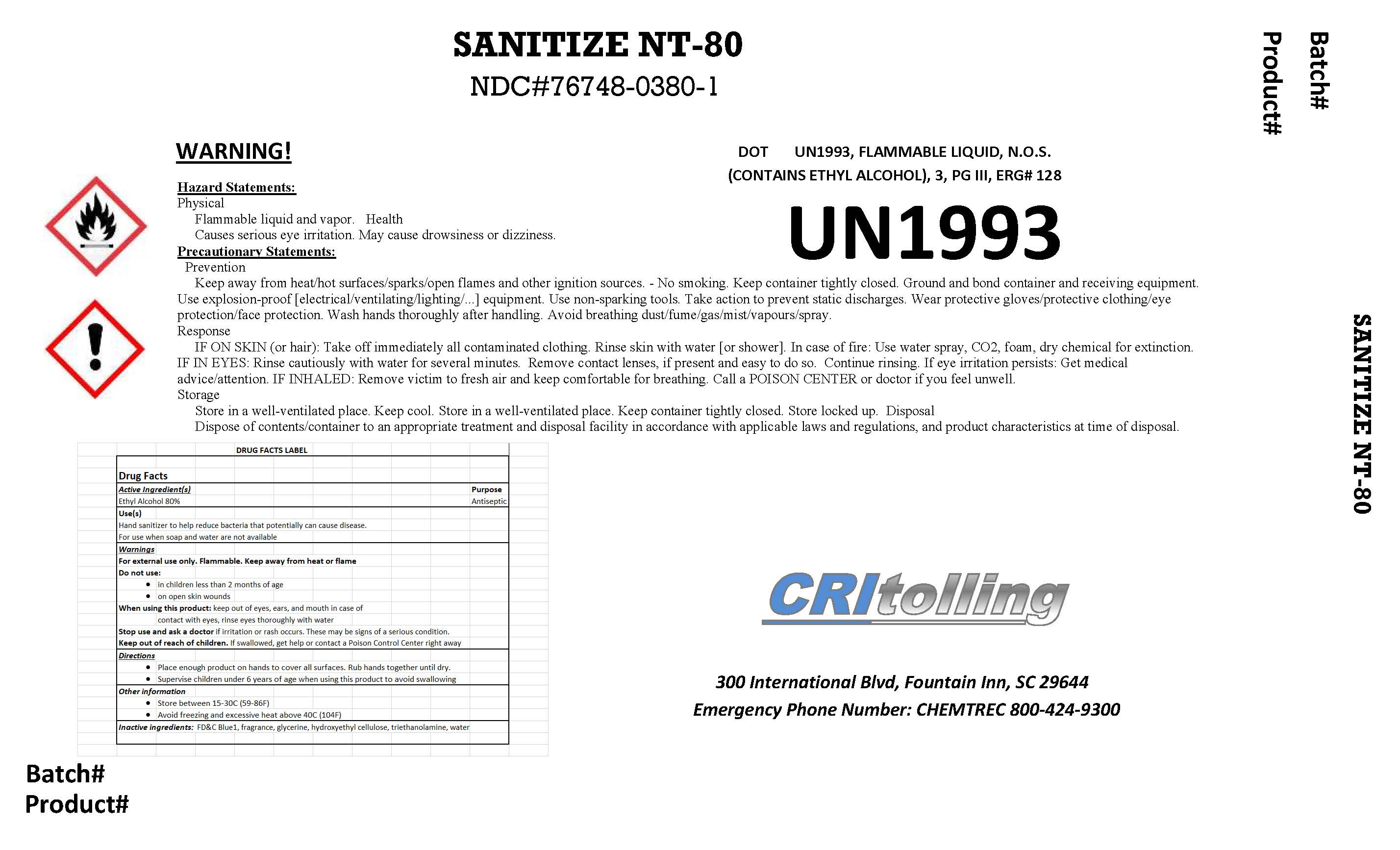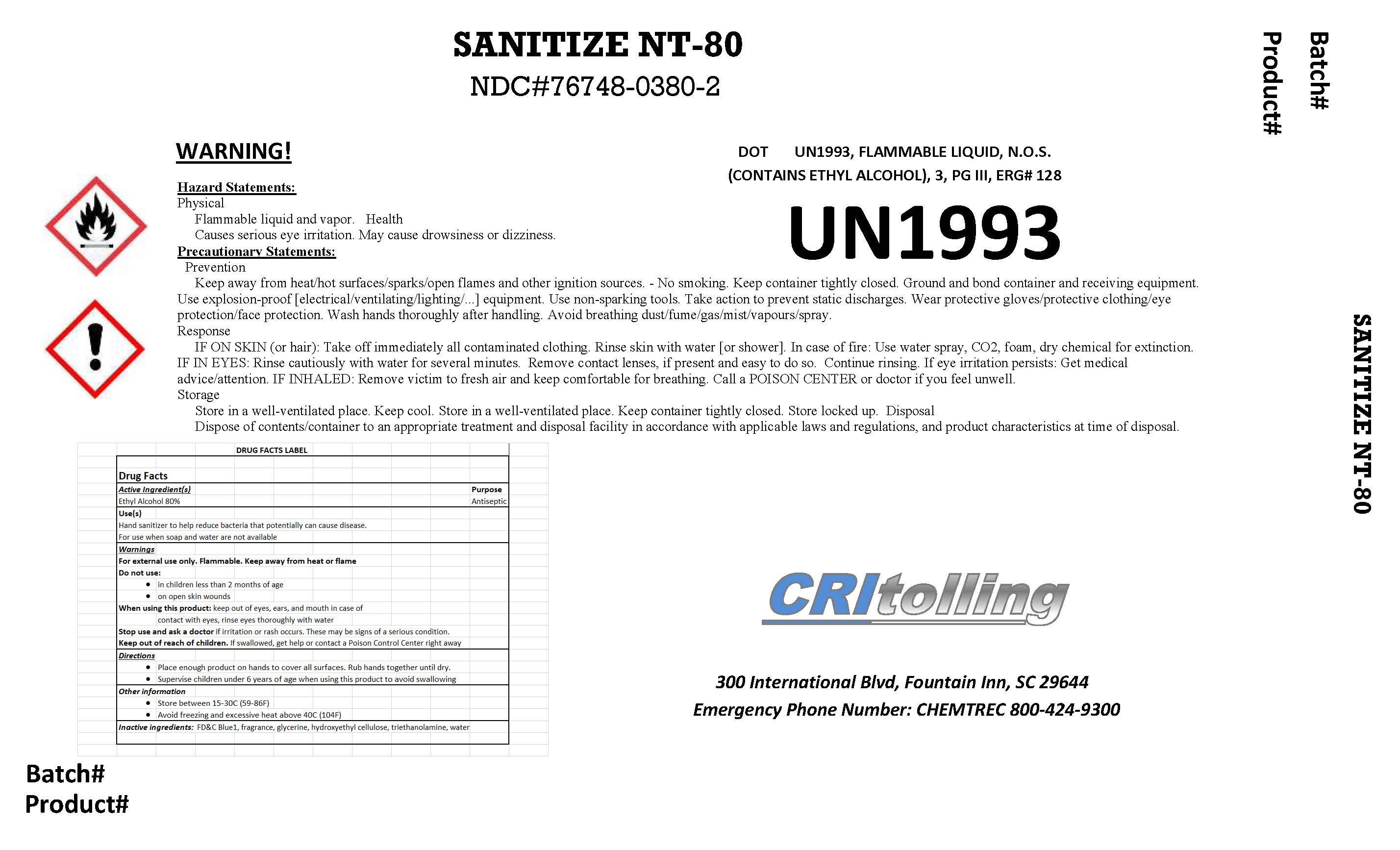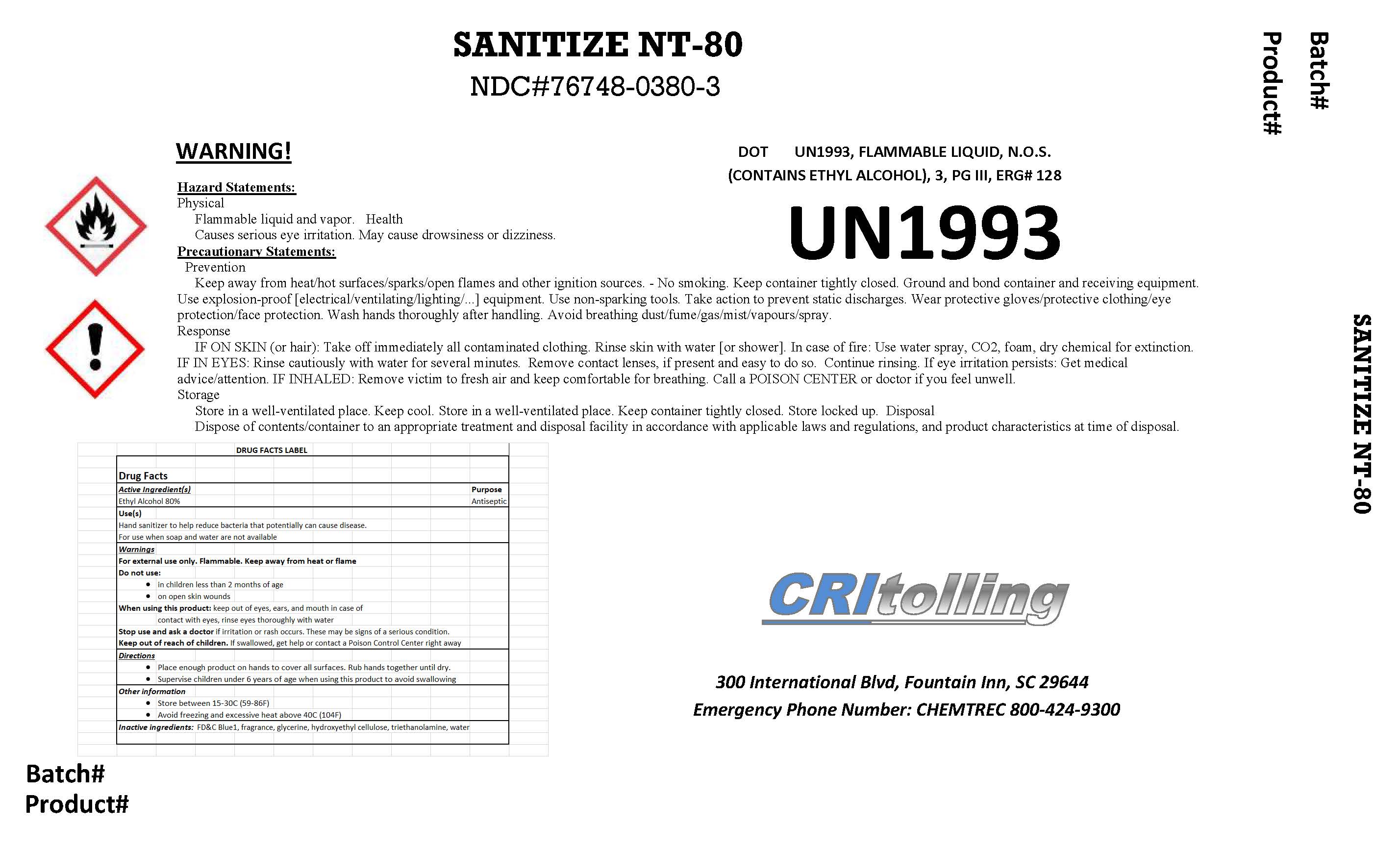 DRUG LABEL: Sanitize NT-75
NDC: 76748-0475 | Form: GEL
Manufacturer: CRI Tolling
Category: otc | Type: HUMAN OTC DRUG LABEL
Date: 20200902

ACTIVE INGREDIENTS: ISOPROPYL ALCOHOL 75 mL/100 mL
INACTIVE INGREDIENTS: HYDROXYETHYL CELLULOSE, UNSPECIFIED 1.8 mL/100 mL; TROLAMINE 0.3 mL/100 mL; FD&C BLUE NO. 1 0.00018 mL/100 mL; GLYCERIN 0.725 mL/100 mL; WATER

CRI Tolling - Sanitize 75 (IPA 75) in drum (1), IBC (2), and pail (3)

This is a hand sanitizer manufactured according to the Temporary Policy for Preparation of Certain Alcohol-Based Hand Sanitizer Products During the Public Health Emergency (CoViD-19); Guidance for Industry.

The hand sanitizer is manufactured using only the following United States Pharmacopoeia (USP) grade ingredients in the preparation of the product (percentage in final product formulation) consistent with World Health Organization (WHO) recommendations:

Sanitize 80

a. Ethanol (80%, v/v) in an aqueous solution denatured according to Alcohol and Tobacco Tax and Trade Bureau regulations in 27 CFR part 20.
b. Glycerol (0.725% v/v).
c. Copolymer (6 % v/v).
d. Trolamine (0.3 % v/v).
e. FD&C Blue No.1 (0.00018 % v/v).
f. Sterile distilled water or boiled cold water.

The firm does not add other active or inactive ingredients. Different or additional ingredients may impact the quality and potency of the product.

Sanitize NT-80

a. Ethanol (80%, v/v) in an aqueous solution denatured according to Alcohol and Tobacco Tax and Trade Bureau regulations in 27 CFR part 20.
b. Glycerol (0.725% v/v).
c. Hydroxyethyl Cellulose (1.8 % v/v).

d. Trolamine (0.3 v/v).

e. FD&C Blue No.1 (0.00018 % v/v).
e. Sterile distilled water or boiled cold water.

The firm does not add other active or inactive ingredients. Different or additional ingredients may impact the quality and potency of the product.

Sanitize 75

a. Isopropyl Alcohol (75%, v/v) in an aqueous solution denatured according to Alcohol and Tobacco Tax and Trade Bureau regulations in 27 CFR part 20.

b. Glycerol (0.725 % v/v).
c. Copolymer (8.2 % v/v).
d. Trolamine (1 % v/v)
e. FD&C Blue No.1 (0.00018 % v/v).
f. Sterile distilled water or boiled cold water.

The firm does not add other active or inactive ingredients. Different or additional ingredients may impact the quality and potency of the product.

Sanitize NT-75

a. Isopropyl Alcohol (75%, v/v) in an aqueous solution denatured according to Alcohol and Tobacco Tax and Trade Bureau regulations in 27 CFR part 20.
b. Glycerol (0.725% v/v).
c. Hydroxyethyl Cellulose (1.8 % v/v).

d. Trolamine (0.3 v/v).

e. FD&C Blue No.1 (0.00018 % v/v).
e. Sterile distilled water or boiled cold water.

The firm does not add other active or inactive ingredients. Different or additional ingredients may impact the quality and potency of the product.

Active Ingredient(s)

Sanitize 75 (NDC# 76748-0275 and Sanitize NT-75 (NDC# 76748-0475)

Isopropyl Alcohol 75% v/v. Purpose: Antiseptic

Sanitize 80 (NDS# 76748-0180) and Sanitize NT-80 (NDC# 76748-0380)

Ethanol 80% v/v. Purpose Antiseptic

Purpose

Antiseptic, Hand Sanitizer

Use

Hand Sanitizer to help reduce bacteria that potentially can cause disease. For use when soap and water are not available.

Warnings

For external use only. Flammable. Keep away from heat or flame

Do not use

- in children less than 2 months of age
- on open skin wounds

When using this product keep out of eyes, ears, and mouth. In case of contact with eyes, rinse eyes thoroughly with water.
Stop use and ask a doctor if irritation or rash occurs. These may be signs of a serious condition.
Keep out of reach of children. If swallowed, get medical help or contact a Poison Control Center right away.

Stop use and ask a doctor if irritation or rash occurs. These may be signs of a serious condition.

Keep out of reach of children. If swallowed, get medical help or contact a Poison Control Center right away.

Directions

- Place enough product on hands to cover all surfaces. Rub hands together until dry.
- Supervise children under 6 years of age when using this product to avoid swallowing.

Other information

- Store between 15-30C (59-86F)
- Avoid freezing and excessive heat above 40C (104F)

Inactive ingredients

glycerin, hydrogen peroxide, purified water USP